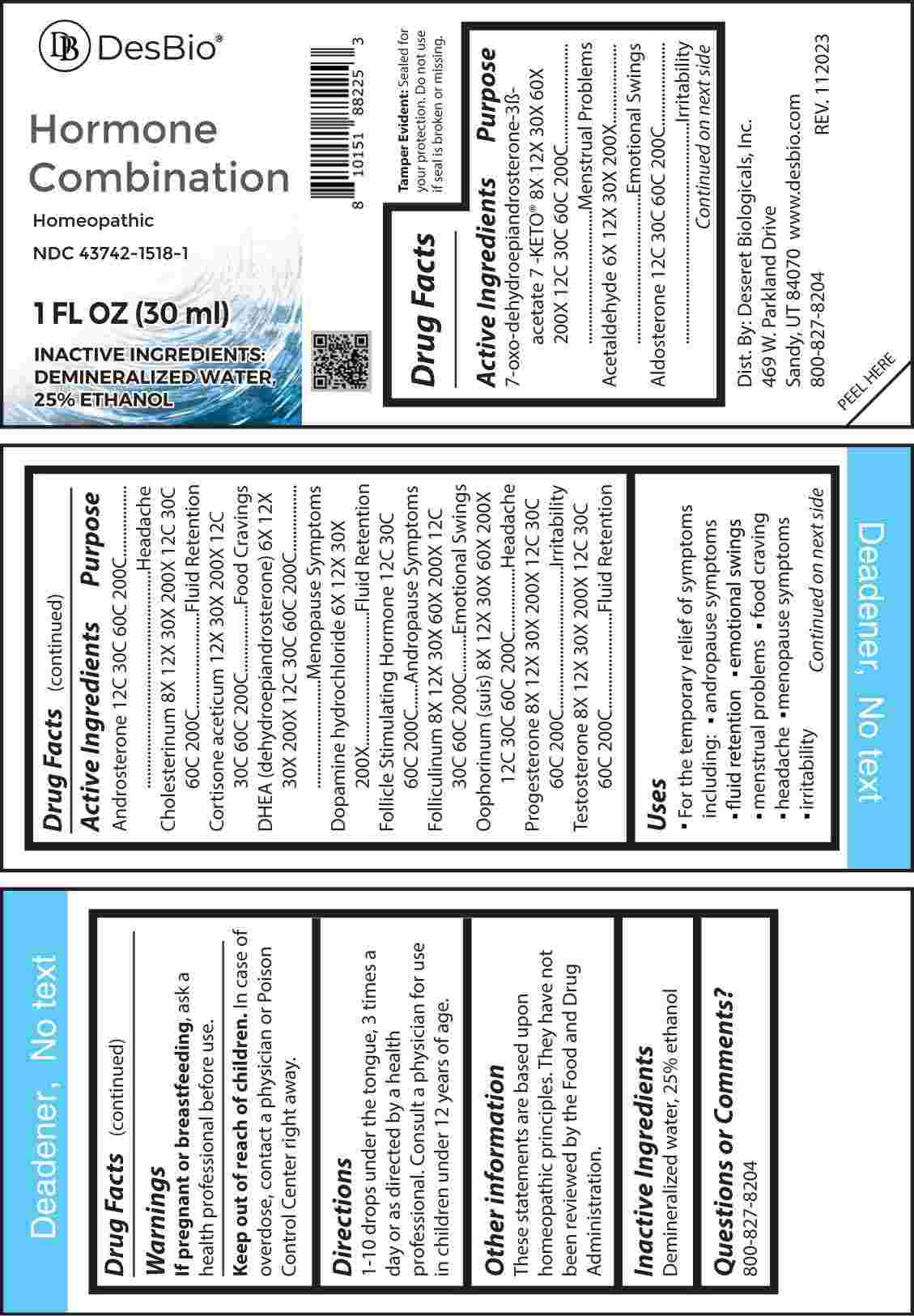 DRUG LABEL: Hormone Combination
NDC: 43742-1518 | Form: LIQUID
Manufacturer: Deseret Biologicals, Inc.
Category: homeopathic | Type: HUMAN OTC DRUG LABEL
Date: 20240311
DEA Schedule: CIII

ACTIVE INGREDIENTS: ACETALDEHYDE 6 [hp_X]/1 mL; DOPAMINE HYDROCHLORIDE 6 [hp_X]/1 mL; PRASTERONE 6 [hp_X]/1 mL; 7-KETO-DEHYDROEPIANDROSTERONE 6 [hp_X]/1 mL; ESTRONE 8 [hp_X]/1 mL; SUS SCROFA OVARY 8 [hp_X]/1 mL; CHOLESTEROL 8 [hp_X]/1 mL; PROGESTERONE 8 [hp_X]/1 mL; TESTOSTERONE 8 [hp_X]/1 mL; CORTISONE ACETATE 12 [hp_X]/1 mL; ALDOSTERONE 12 [hp_C]/1 mL; ANDROSTERONE 12 [hp_C]/1 mL; FOLLITROPIN 12 [hp_C]/1 mL
INACTIVE INGREDIENTS: WATER; ALCOHOL

DRUG FACTS:

ACTIVE INGREDIENTS:

7-Oxo-Dehydroepiandrosterone 3β-Acetate, 8X, 12X, 30X, 60X, 200X, 12C, 30C, 60C, 200C, Acetaldehyde 6X, 12X, 30X, 200X, Aldosterone 12C, 30C, 60C, 200C, Androsterone 12C, 30C, 60C, 200C, Cholesterinum 8X, 12X, 30X, 200X, 12C, 30C, 60C, 200C, Cortisone Aceticum 12X, 30X, 200X, 12C, 30C, 60C, 200C, DHEA (Dehydroepiandrosterone) 6X, 12X, 30X, 200X, 12C, 30C, 60C, 200C, Dopamine Hydrochloride 6X, 12X, 30X, 200X, Follicle Stimulating Hormone 12C, 30C, 60C, 200C, Folliculinum 8X, 12X, 30X, 60X, 200X, 12C, 30C, 60C, 200C, Oophorinum (Suis) 8X, 12X, 30X, 60X, 200X, 12C, 30C, 60C, 200C, Progesterone 8X, 12X, 30X, 200X, 12C, 30C, 60C, 200C, Testosterone 8X, 12X, 30X, 200X, 12C, 30C, 60C, 200C.

PURPOSE:

7-Oxo-Dehydroepiandrosterone 3β-Acetate – Menstrual Problems, Acetaldehyde – Emotional Swings, Aldosterone - Irritability, Androsterone - Headache, Cholesterinum – Fluid Retention, Cortisone Aceticum – Food Cravings, DHEA – Menopausal Symptoms, Dopamine Hydrochloride – Fluid Retention, Follicle Stimulating Hormone – Andropausal Symptoms, Folliculinum – Emotional Swings, Oophorinum - Headache, Progesterone – Irritability, Testosterone – Fluid Retention

USES:

• For the temporary relief of symptoms including:

• andropause symptoms • fluid retention • emotional swings

• menstrual problems • food craving

• headache • menopause symptoms

• irritability

These statements are based upon homeopathic principles. They have not been reviewed by the Food and Drug Administration.

WARNINGS:

If pregnant or breast-feeding, ask a health professional before use.

Keep out of reach of children. In case of overdose, contact a physician or Poison Control Center right away.

Tamper Evident: Sealed for your protection. Do not use if seal is broken or missing.

KEEP OUT OF REACH OF CHILDREN:

In case of overdose, contact a physician or Poison Control Center right away.

DIRECTIONS:

1-10 drops under the tongue, 3 times a day or as directed by a health professional. Consult a physician for use in children under 12 years of age.

INACTIVE INGREDIENTS:

Demineralized water, 25% ethanol

QUESTIONS:

Dist. By: Deseret Biologicals, Inc.
469 W. Parkland Drive
Sandy, UT 84070

www.desbio.com

800-827-8204

PACKAGE LABEL DISPLAY:

Des Bio

Hormone

Combination

Homeopathic

NDC 43742-1518-1

1 FL OZ (30 ml)